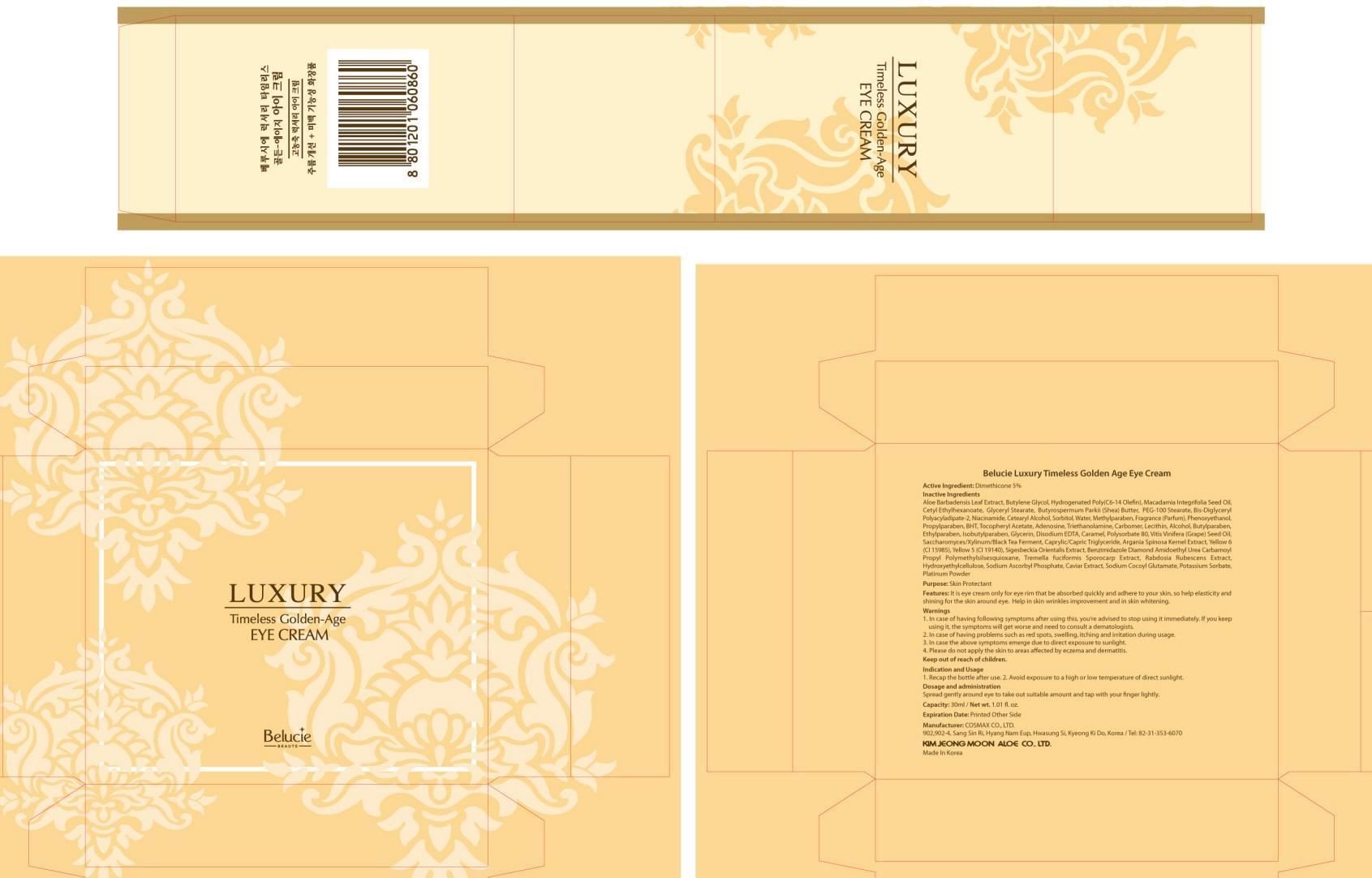 DRUG LABEL: Belucie Luxury Timeless Golden Age Eye
NDC: 50410-050 | Form: CREAM
Manufacturer: KIMJEONGMOON ALOE CO., LTD.
Category: otc | Type: HUMAN OTC DRUG LABEL
Date: 20121129

ACTIVE INGREDIENTS: Dimethicone 1.5 g/30 mL
INACTIVE INGREDIENTS: ALOE VERA LEAF; Butylene Glycol; Cetyl Ethylhexanoate; SHEA BUTTER

ACTIVE INGREDIENT

Active Ingredient: Dimethicone 5%

INACTIVE INGREDIENT

Inactive Ingredients:
Aloe Barbadensis Leaf Extract, Butylene Glycol, Hydrogenated Poly(C6-14 Olefin),Macadamia Integrifolia Seed Oil,Cetyl Ethylhexanoate,Glyceryl Stearate,Butyrospermum Parkii (Shea) Butter,PEG-100 Stearate,Bis-Diglyceryl Polyacyladipate-2,Niacinamide,Cetearyl Alcohol,Sorbitol,Water,Methylparaben,Fragrance(Parfum), Phenoxyethanol,Propylparaben,BHT,Tocopheryl Acetate,Adenosine,Triethanolamine,Carbomer,Lecithin,Alcohol, Butylparaben,Ethylparaben,Isobutylparaben,Glycerin,Disodium EDTA,Caramel,Polysorbate 80,Vitis Vinifera (Grape) Seed Oil,Saccharomyces/Xylinum/Black Tea Ferment,Caprylic/Capric Triglyceride,Argania Spinosa Kernel Extract,Yellow 6 (CI 15985),Yellow 5 (CI 19140),Sigesbeckia Orientalis Extract,Benzimidazole Diamond Amidoethyl Urea Carbamoyl Propyl Polymethylsilsesquioxane,Tremella fuciformis Sporocarp Extract,Rabdosia Rubescens Extract,Hydroxyethylcellulose,
Sodium Ascorbyl Phosphate,Caviar Extract,Sodium Cocoyl Glutamate,Potassium Sorbate,Platinum Powder

PURPOSE

Purpose: Skin Protectant

WARNINGS

1. In case of having following symptoms after using this, you’re advised to stop using it immediately. If you keep using it, the symptoms will get worse and need to consult a dematologists.
2. In case of having problems such as red spots, swelling, itching and irritation during usage
3. In case the above symptoms emerge due to direct exposure to sunlight
4. Please do not apply the skin to areas affected by eczema and dermatitis

KEEP OUT OF REACH OF CHILDREN

INDICATIONS AND USAGE

Indication and usage
1. Recap the bottle after use.
2. Avoid exposure to a high or low temperature of direct sunlight

DOSAGE AND ADMINISTRATION

Spread gently around eye to take out suitable amount and tap with your finger lightly